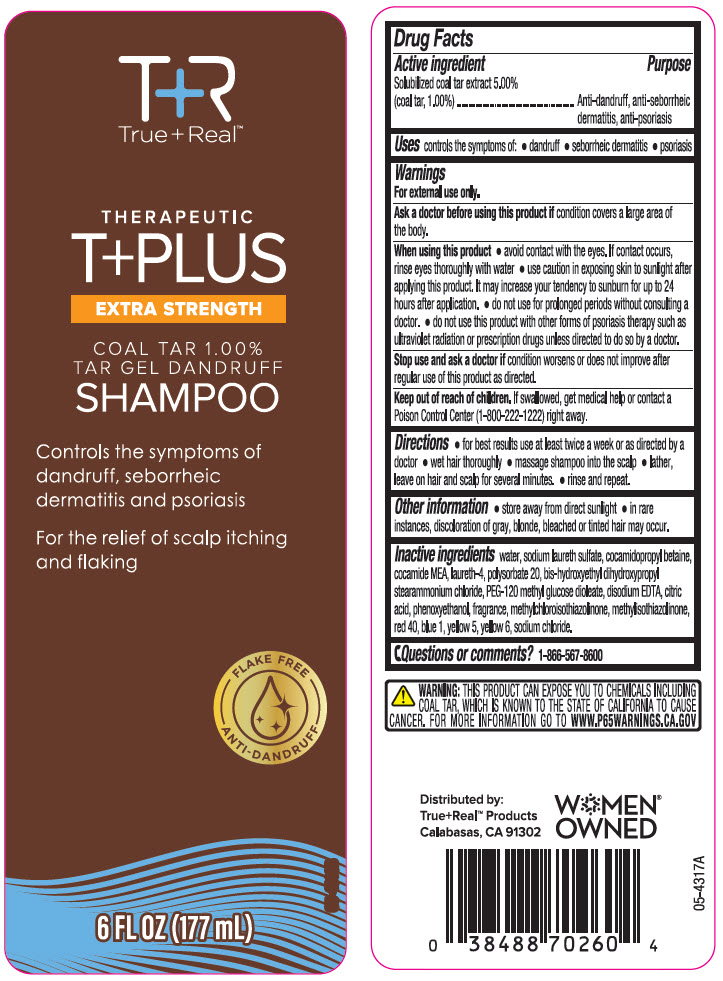 DRUG LABEL: True Plus Real Therapeutic T PLUS EXTRA STRENGTH COAL TAR TAR DANDRUFF
NDC: 67385-260 | Form: SHAMPOO
Manufacturer: Garcoa, Inc.
Category: otc | Type: HUMAN OTC DRUG LABEL
Date: 20240510

ACTIVE INGREDIENTS: COAL TAR 10 mg/1 mL
INACTIVE INGREDIENTS: Water; SODIUM LAURYL SULFATE; Cocamidopropyl Betaine; COCO MONOETHANOLAMIDE; Laureth-4; Polysorbate 20; Bis-Hydroxyethyl Dihydroxypropyl Stearammonium Chloride; PEG-120 Methyl Glucose Dioleate; EDETATE DISODIUM; CITRIC ACID MONOHYDRATE; Phenoxyethanol; Methylchloroisothiazolinone; Methylisothiazolinone; FD&C RED NO. 40; FD&C BLUE NO. 1; FD&C YELLOW NO. 5; FD&C YELLOW NO. 6; Sodium Chloride

True+Real™ Therapeutic T+PLUS EXTRA STRENGTH COAL TAR 1.00% TAR GEL DANDRUFF SHAMPOO
Anti-dandruff, anti-seborrheic dermatitis, anti-psoriasis

Drug Facts

Active ingredient

Solubilized Coal Tar Extract 5.00% (Coal Tar, 1.00%)

Purpose

Anti-dandruff, anti-seborrheic dermatitis, anti-psoriasis

Use

controls the symptom of:

- dandruff
- seborrheic dermatitis
- psoriasis

Warnings

For external use only.

Ask a doctor before using this product if condition covers a large area of the body.

When using this product

- avoid contact with the eyes. If contact occurs, rinse eyes thoroughly with water
- use caution in exposing skin to sunlight after applying this product. It may increase your tendency to sunburn for up to 24 hours after application.
- do not use for prolonged periods without consulting a doctor.
- do not use this product with other forms of psoriasis therapy such as ultraviolet radiation or prescription drugs unless directed to do so by a doctor.

Stop use and ask a doctor if condition worsens or does not improve after regular use of this product as directed.

Keep out of reach of children. If swallowed, get medical help or contact a Poison Control Center (1-800-222-1222) right away.

Directions

- for best results use at least twice a week or as directed by a doctor
- wet hair thoroughly
- massage shampoo into the scalp
- lather, leave on hair and scalp for several minutes.
- rinse and repeat

Other information

- store away from direct sunlight
- in rare instances, discoloration of gray, blonde, bleached or tinted hair may occur

Inactive ingredients

water, sodium laureth sulfate, cocamidopropyl betaine, cocamide MEA, laureth-4, polysorbate 20, bis-hydroxyethyl dihydroxypropyl stearammonium chloride, PEG-120 methyl glucose dioleate, disodium EDTA, citric acid, phenoxyethanol, fragrance, methylchloroisothiazolinone, methylisothiazolinone, red 40, blue 1, yellow 5, yellow 6, sodium chloride.

Questions or comments?

1-866-567-8600

Distributed by:
True+Real™ Products
Calabasas, CA 91302

PRINCIPAL DISPLAY PANEL - 177 mL Bottle Label

True+Real™

THERAPEUTIC
T+PLUS
EXTRA STRENGTH

COAL TAR 1.00%
TAR GEL DANDRUFF
SHAMPOO

Controls the symptoms of
dandruff, seborrheic
dermatitis and psoriasis

For the relief of scalp itching
and flaking

FLAKE FREE
ANTI-DANDRUFF

6 FL OZ (177 mL)